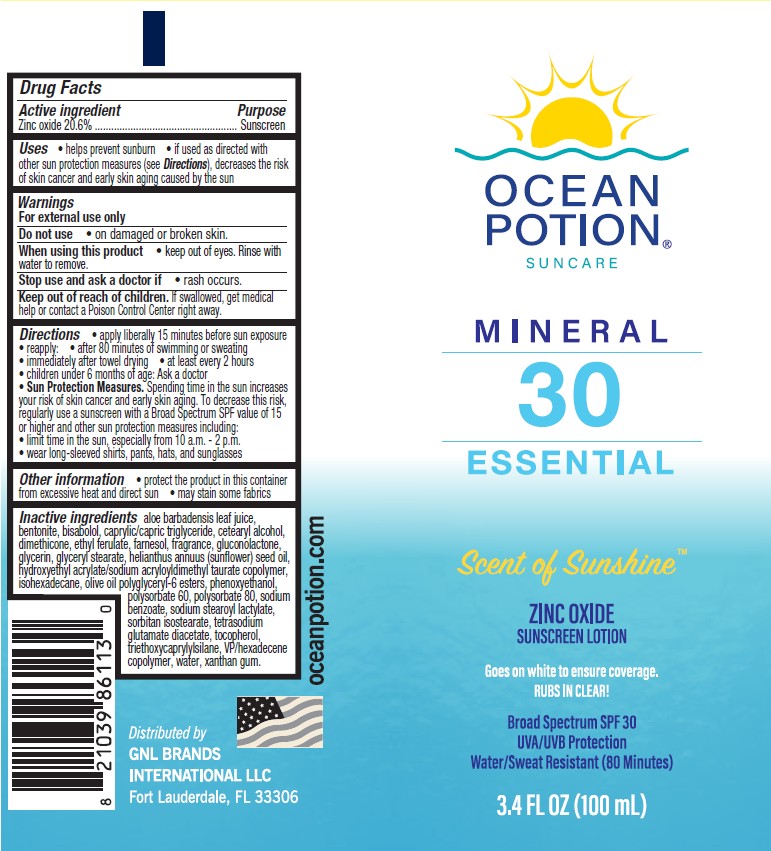 DRUG LABEL: Ocean Potion Suncare Mineral 30 Essential Scent of Sunshine Zinc Oxide Sunscreen
NDC: 85638-009 | Form: LOTION
Manufacturer: GNL BRANDS INTERNATIONAL, LLC
Category: otc | Type: HUMAN OTC DRUG LABEL
Date: 20250831

ACTIVE INGREDIENTS: ZINC OXIDE 206 mg/1 mL
INACTIVE INGREDIENTS: TRIETHOXYCAPRYLYLSILANE; BENTONITE; OLIVE OIL POLYGLYCERYL-6 ESTERS; ALOE VERA LEAF; GLYCERYL 1-STEARATE; CETOSTEARYL ALCOHOL; .ALPHA.-TOCOPHEROL, DL-; VINYLPYRROLIDONE/HEXADECENE COPOLYMER; WATER; MEDIUM-CHAIN TRIGLYCERIDES; GLYCERIN; PHENOXYETHANOL; HEXAMETHYLDISILOXANE; SORBITAN ISOSTEARATE; POLYSORBATE 80; HYDROXYETHYL ACRYLATE/SODIUM ACRYLOYLDIMETHYL TAURATE COPOLYMER (100000 MPA.S AT 1.5%); XANTHAN GUM; SODIUM STEAROYL LACTYLATE; SODIUM BENZOATE; LEVOMENOL; POLYSORBATE 60; TETRASODIUM GLUTAMATE DIACETATE; FARNESOL; ISOHEXADECANE; SUNFLOWER OIL; ETHYL FERULATE; GLUCONOLACTONE

Ocean Potion Suncare Mineral 30 Essential Scent of Sunshine Zinc Oxide Sunscreen Lotion

Active ingredients

Zinc Oxide 20.6%

Purpose

Sunscreen

Uses

• helps prevent sunburn • if used as directed with other sun protection measures (see Directions), decreases the risk of skin cancer and early skin aging caused by the sun

Warnings

For external use only

Do not use

• on damaged or broken skin

When using this product

• keep out of eyes. Rinse with water to remove.

Stop use and ask a doctor if

- rash occurs

Keep out of reach of children.

If swallowed, get medical help or contact a Poison Control Center right away.

Directions

• apply liberally 15 minutes before sun exposure

• reapply:

• after 80 minutes of swimming or sweating

• immediately after towel drying

• at least every 2 hours

• children under 6 months of age: Ask a doctor

- Sun Protection Measures. Spending time in the sun increases your risk of skin cancer and early skin aging. To decrease this risk, regularly use a sunscreen with a Broad Spectrum SPF value of 15 or higher and other sun protection measures including:

• limit time in the sun, especially from 10 a.m. - 2 p.m.

• wear long-sleeved shirts, pants, hats, and sunglasses

Other information

• protect the product in this container from excessive heat and direct sun

• may stain or damage some fabrics, materials or surfaces

Inactive ingredients

aloe barbadensis leaf juice, bentonite, bisabolol,
caprylic/capric triglyceride, cetearyl alcohol, dimethicone, ethyl ferulate, farnesol, fragrance,
gluconolactone, glycerin, glyceryl stearate, helianthus annuus (sunflower) seed oil,
hydroxyethyl acrylate/sodium acryloyldimethyl taurate copolymer, isohexadecane,
olive oil polyglyceryl-6 esters, phenoxyethanol, polysorbate 60, polysorbate 80,
sodium benzoate, sodium stearoyl lactylate, sorbitan isostearate, tetrasodium
glutamate diacetate, tocopherol, triethoxycaprylylsilane, VP/hexadecene
copolymer, water, xanthan gum